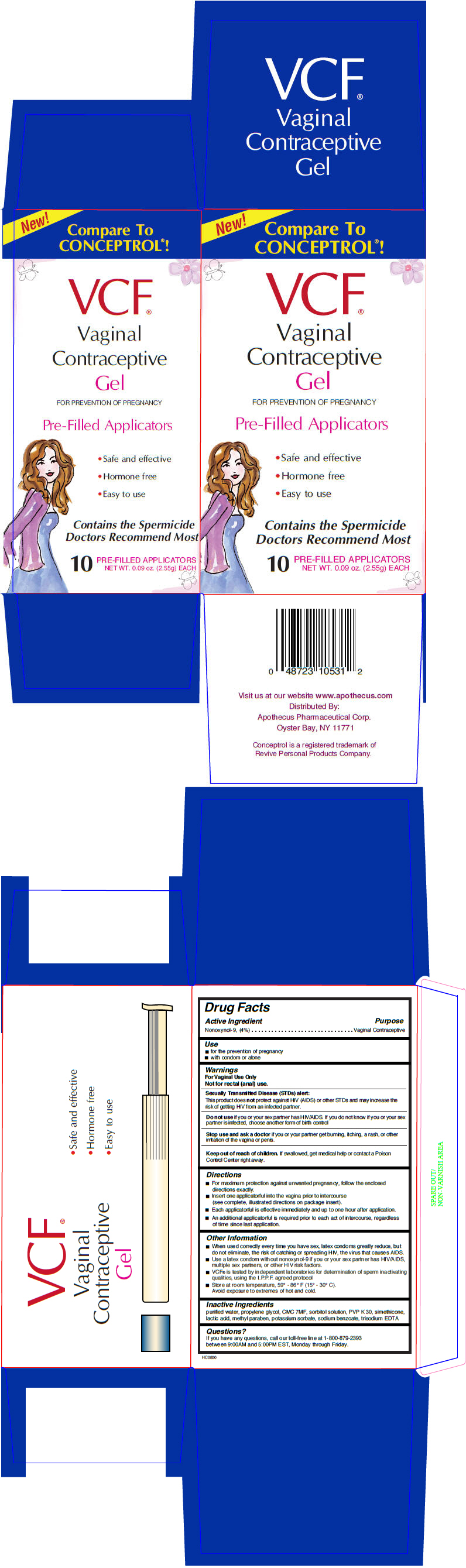 DRUG LABEL: VCF CONTRACEPTIVE PRE-FILLED APPLICATORS
NDC: 52925-512 | Form: GEL, METERED
Manufacturer: APOTHECUS PHARMACEUTICAL CORP
Category: otc | Type: HUMAN OTC DRUG LABEL
Date: 20251212

ACTIVE INGREDIENTS: NONOXYNOL-9 4 g/100 g
INACTIVE INGREDIENTS: Water; Propylene Glycol; Sodium Benzoate; Sorbitol; Povidone K30; Lactic Acid, Unspecified Form; Methylparaben; Potassium Sorbate; Edetate Trisodium

VCF® CONTRACEPTIVE GEL PRE-FILLED APPLICATORS

Drug Facts

Active Ingredient

Nonoxynol-9, (4%)

Purpose

Vaginal Contraceptive

Use

- for the prevention of pregnancy
- with condom or alone

Warnings

For Vaginal Use Only

Not for rectal (anal) use.

Sexually Transmitted Disease (STDs) alert

This product does not protect against HIV (AIDS) or other STDs and may increase the risk of getting HIV from an infected partner.

Do not use if you or your sex partner has HIV/AIDS. If you do not know if you or your sex partner is infected, choose another form of birth control

Stop use and ask a doctor if you or your partner get burning, itching, a rash, or other irritation of the vagina or penis.

Keep out of reach of children. If swallowed, get medical help or contact a Poison Control Center right away.

Directions

- For maximum protection against unwanted pregnancy, follow the enclosed directions exactly.
- Insert one applicatorful into the vagina prior to intercourse (see complete, illustrated directions on package insert).
- Each applicatorful is effective immediately and up to one hour after application.
- An additional applicatorful is required prior to each act of intercourse, regardless of time since last application.

Other Information

- When used correctly every time you have sex, latex condoms greatly reduce, but do not eliminate, the risk of catching or spreading HIV, the virus that causes AIDS.
- Use a latex condom without nonoxynol-9 if you or your sex partner has HIV/AIDS, multiple sex partners, or other HIV risk factors.
- VCF® is tested by independent laboratories for determination of sperm inactivating qualities, using the I.P.P.F. agreed protocol
- Store at room temperature, 59° - 86° F (15° - 30° C).
  Avoid exposure to extremes of hot and cold.

Inactive Ingredients

purified water, propylene glycol, CMC 7MF, sorbitol solution, PVP K 30, simethicone, lactic acid, methyl paraben, potassium sorbate, sodium benzoate, trisodium EDTA

Questions?

If you have any questions, call our toll-free line at 1-800-879-2393 between 9:00AM and 5:00PM EST, Monday through Friday.

Distributed By:
Apothecus Pharmaceutical Corp.
Oyster Bay, NY 11771

PRINCIPAL DISPLAY PANEL - 2.55 g Applicator Box

New!

Compare To
CONCEPTROL®!

VCF®

Vaginal
Contraceptive
Gel

FOR PREVENTION OF PREGNANCY

Pre-Filled Applicators

- Safe and effective
- Hormone free
- Easy to use

Contains the Spermicide
Doctors Recommend Most

10
PRE-FILLED APPLICATORS
NET WT. 0.09 oz. (2.55g) EACH